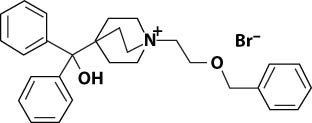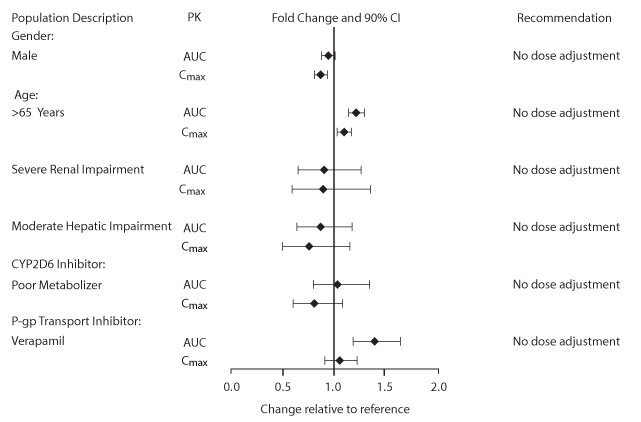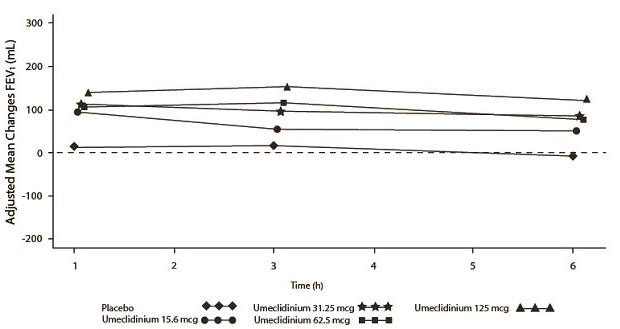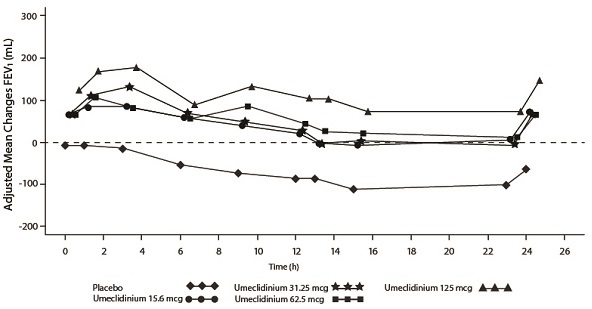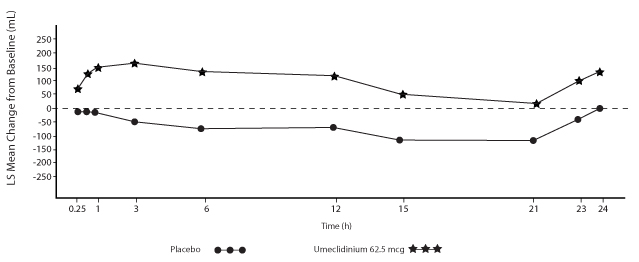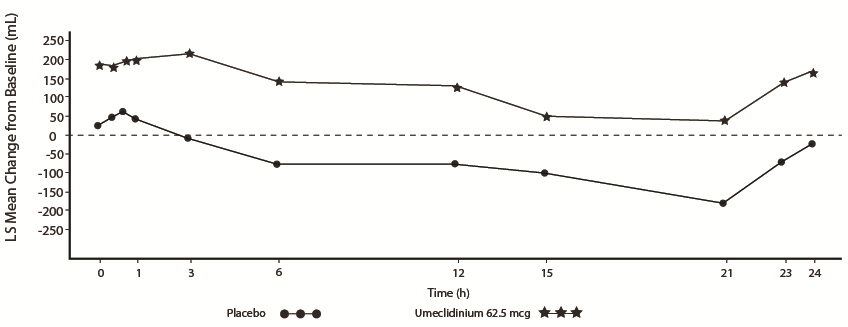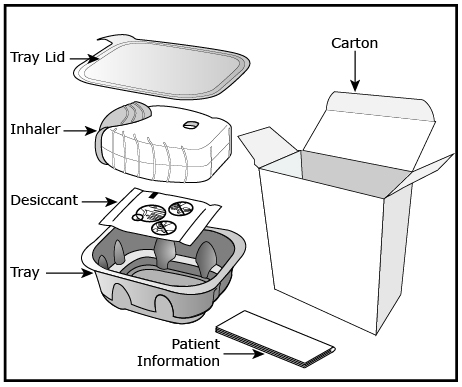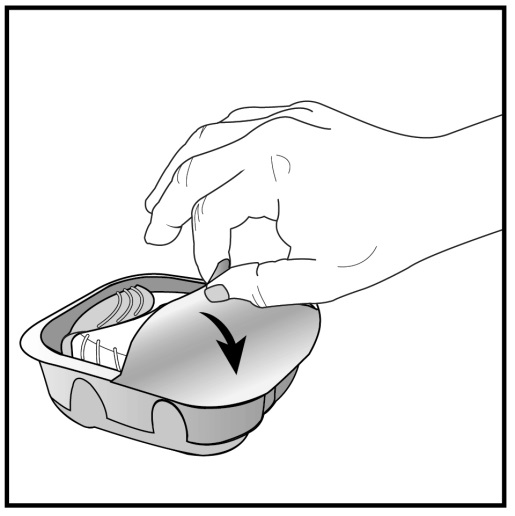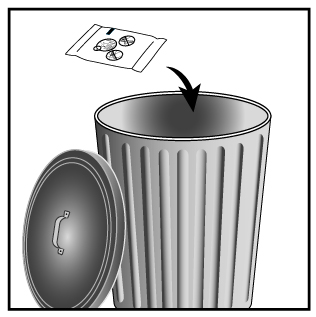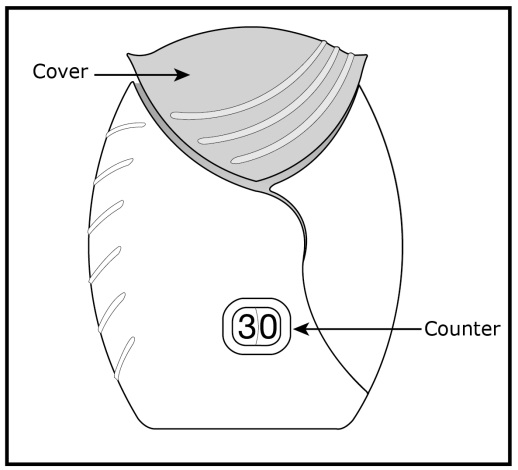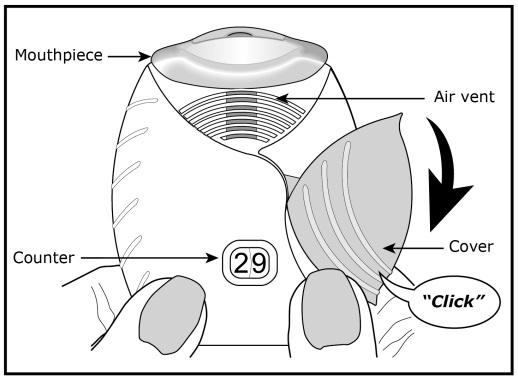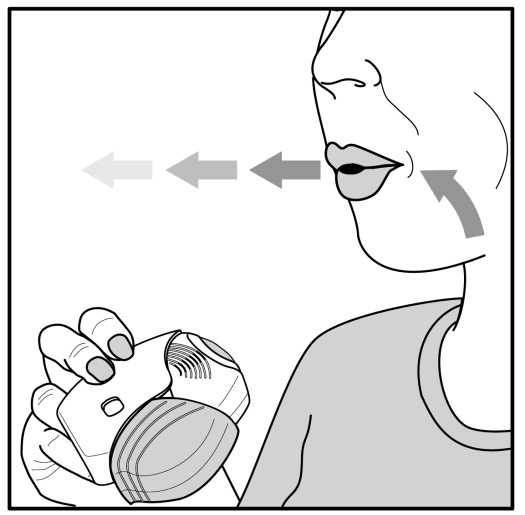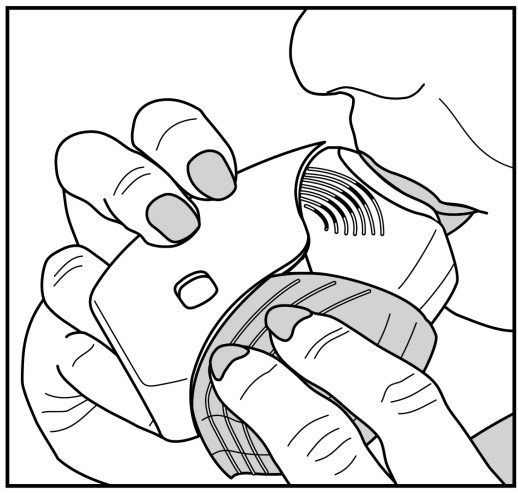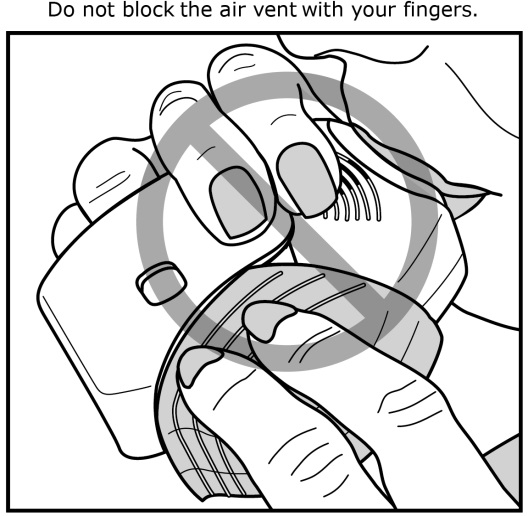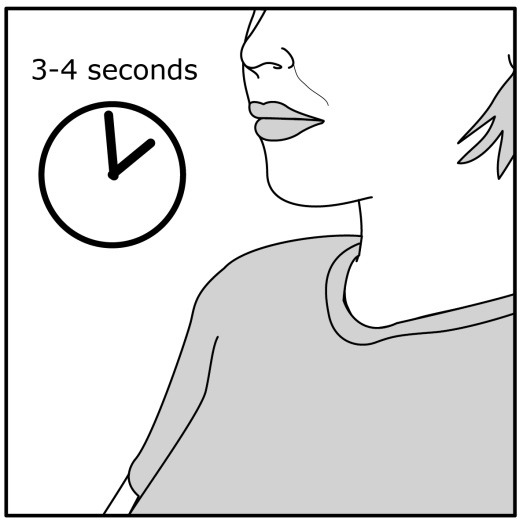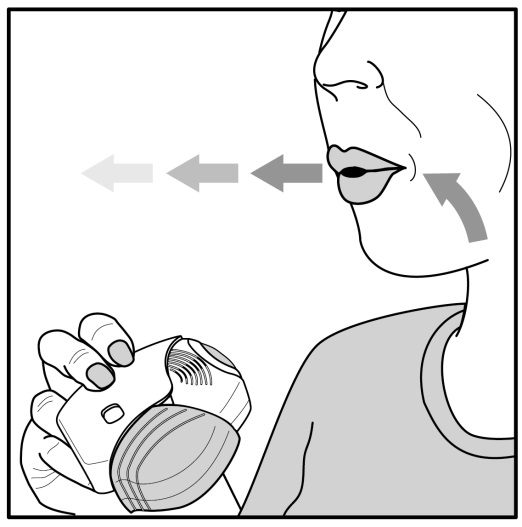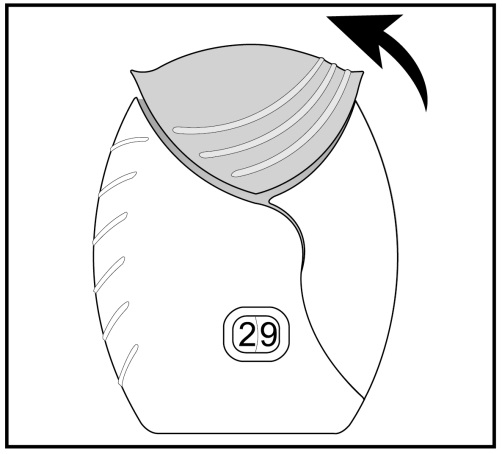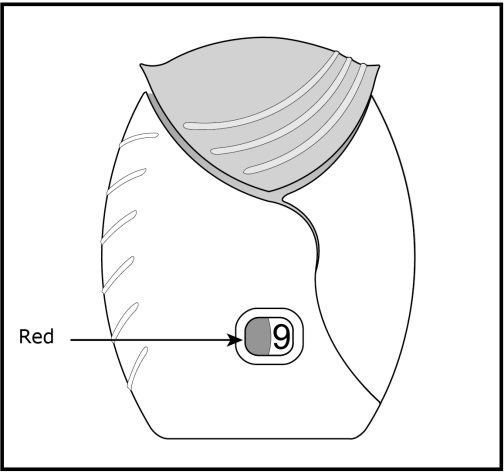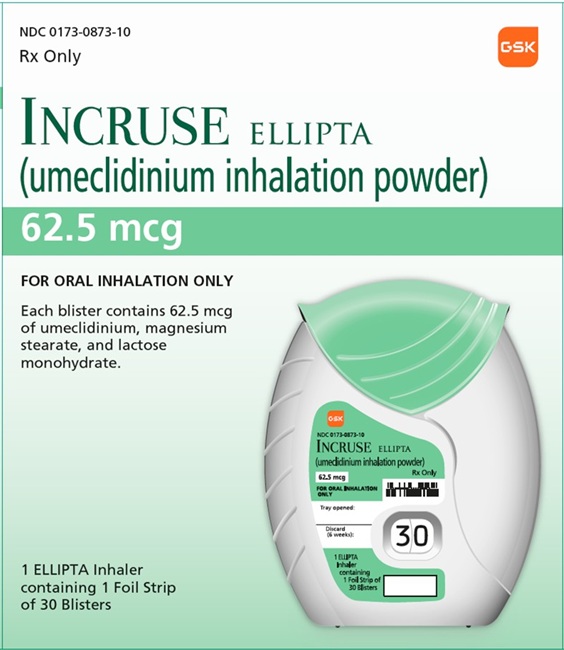 DRUG LABEL: Incruse Ellipta
NDC: 0173-0873 | Form: AEROSOL, POWDER
Manufacturer: GlaxoSmithKline LLC
Category: prescription | Type: HUMAN PRESCRIPTION DRUG LABEL
Date: 20231213

ACTIVE INGREDIENTS: UMECLIDINIUM BROMIDE 62.5 ug/1 1
INACTIVE INGREDIENTS: MAGNESIUM STEARATE; LACTOSE MONOHYDRATE

HIGHLIGHTS OF PRESCRIBING INFORMATION

These highlights do not include all the information needed to use INCRUSE ELLIPTA safely and effectively. See full prescribing information for INCRUSE ELLIPTA.
INCRUSE ELLIPTA (umeclidinium inhalation powder), for oral inhalation use
Initial U.S. Approval: 2013

1 INDICATIONS AND USAGE

INCRUSE ELLIPTA is an anticholinergic indicated for the maintenance treatment of patients with chronic obstructive pulmonary disease (COPD). (1)

2 DOSAGE AND ADMINISTRATION

- For oral inhalation only. (2)
- Maintenance treatment of COPD: 1 actuation of INCRUSE ELLIPTA once daily administered by oral inhalation. (2)

3 DOSAGE FORMS AND STRENGTHS

Inhalation powder: 62.5 mcg of umeclidinium per actuation. (3)

4 CONTRAINDICATIONS

- Severe hypersensitivity to milk proteins. (4)
- Hypersensitivity to any ingredient. (4)

5 WARNINGS AND PRECAUTIONS

- Do not initiate in acutely deteriorating COPD. Do not use to treat acute symptoms. (5.1)
- If paradoxical bronchospasm occurs, discontinue INCRUSE ELLIPTA and institute alternative therapy. (5.2)
- Worsening of narrow-angle glaucoma may occur. Use with caution in patients with narrow-angle glaucoma and instruct patients to contact a healthcare provider immediately if symptoms occur. (5.4)
- Worsening of urinary retention may occur. Use with caution in patients with prostatic hyperplasia or bladder-neck obstruction and instruct patients to contact a healthcare provider immediately if symptoms occur. (5.5)

6 ADVERSE REACTIONS

Most common adverse reactions (incidence ≥2% and more common than placebo) include nasopharyngitis, upper respiratory tract infection, cough, arthralgia. (6.1)

To report SUSPECTED ADVERSE REACTIONS, contact GlaxoSmithKline at 1-888-825-5249 or FDA at 1-800-FDA-1088 or www.fda.gov/medwatch.

7 DRUG INTERACTIONS

Anticholinergics: May interact additively with concomitantly used anticholinergic medications. Avoid administration of INCRUSE ELLIPTA with other anticholinergic-containing drugs. (7.1)

FULL PRESCRIBING INFORMATION

1 INDICATIONS AND USAGE

INCRUSE ELLIPTA is indicated for the maintenance treatment of patients with chronic obstructive pulmonary disease (COPD).

2 DOSAGE AND ADMINISTRATION

The recommended dosage of INCRUSE ELLIPTA for maintenance treatment of COPD is 1 actuation (umeclidinium 62.5 mcg) once daily by oral inhalation.

- INCRUSE ELLIPTA should be used at the same time every day. Do not use INCRUSE ELLIPTA more than 1 time every 24 hours.
- No dosage adjustment is required for geriatric patients, patients with renal impairment, or patients with moderate hepatic impairment [see Clinical Pharmacology (12.3)].

3 DOSAGE FORMS AND STRENGTHS

Inhalation powder: 62.5 mcg umeclidinium per actuation.

4 CONTRAINDICATIONS

INCRUSE ELLIPTA is contraindicated in the following conditions:

- Severe hypersensitivity to milk proteins [see Warnings and Precautions (5.3)]
- Hypersensitivity to umeclidinium or any of the excipients [see Warnings and Precautions (5.3), Description (11)]

5 WARNINGS AND PRECAUTIONS

5.1 Deterioration of Disease and Acute Episodes

INCRUSE ELLIPTA should not be initiated in patients during rapidly deteriorating or potentially life-threatening episodes of COPD. INCRUSE ELLIPTA has not been studied in subjects with acutely deteriorating COPD. The initiation of INCRUSE ELLIPTA in this setting is not appropriate.

INCRUSE ELLIPTA should not be used for the relief of acute symptoms, i.e., as rescue therapy for the treatment of acute episodes of bronchospasm. INCRUSE ELLIPTA has not been studied in the relief of acute symptoms and extra doses should not be used for that purpose. Acute symptoms should be treated with an inhaled, short-acting beta2-agonist.

If INCRUSE ELLIPTA no longer controls symptoms of bronchoconstriction; the patient’s inhaled, short-acting beta2-agonist becomes less effective; or the patient needs more short-acting beta2-agonist than usual, these may be markers of deterioration of disease. In this setting re-evaluate the patient and the COPD treatment regimen at once. Increasing the daily dose of INCRUSE ELLIPTA beyond the recommended dose is not appropriate in this situation.

5.2 Paradoxical Bronchospasm

As with other inhaled therapies, INCRUSE ELLIPTA can produce paradoxical bronchospasm, which may be life threatening. If paradoxical bronchospasm occurs following dosing with INCRUSE ELLIPTA, it should be treated immediately with an inhaled, short-acting bronchodilator; INCRUSE ELLIPTA should be discontinued immediately; and alternative therapy should be instituted.

5.3 Hypersensitivity Reactions, including Anaphylaxis

Hypersensitivity reactions such as anaphylaxis, angioedema, pruritus, rash, and urticaria may occur after administration of INCRUSE ELLIPTA. Discontinue INCRUSE ELLIPTA if such reactions occur. There have been reports of anaphylactic reactions in patients with severe milk protein allergy after inhalation of other powder medications containing lactose; therefore, patients with severe milk protein allergy should not use INCRUSE ELLIPTA [see Contraindications (4), Adverse Reactions (6.2)].

5.4 Worsening of Narrow-Angle Glaucoma

INCRUSE ELLIPTA should be used with caution in patients with narrow-angle glaucoma. Prescribers and patients should also be alert for signs and symptoms of acute narrow-angle glaucoma (e.g., eye pain or discomfort, blurred vision, visual halos or colored images in association with red eyes from conjunctival congestion and corneal edema). Instruct patients to consult a healthcare provider immediately if any of these signs or symptoms develop.

5.5 Worsening of Urinary Retention

INCRUSE ELLIPTA, like all therapies containing an anticholinergic, should be used with caution in patients with urinary retention. Prescribers and patients should be alert for signs and symptoms of urinary retention (e.g., difficulty passing urine, painful urination), especially in patients with prostatic hyperplasia or bladder-neck obstruction. Instruct patients to consult a healthcare provider immediately if any of these signs or symptoms develop.

6 ADVERSE REACTIONS

The following adverse reactions are described in greater detail in other sections:

- Paradoxical bronchospasm [see Warnings and Precautions (5.2)]
- Worsening of narrow-angle glaucoma [see Warnings and Precautions (5.4)]
- Worsening of urinary retention [see Warnings and Precautions (5.5)]

6.1 Clinical Trials Experience

Because clinical trials are conducted under widely varying conditions, adverse reaction rates observed in the clinical trials of a drug cannot be directly compared with rates in the clinical trials of another drug and may not reflect the rates observed in practice.

In the 8 clinical trials conducted to support initial approval of INCRUSE ELLIPTA, a total of 1,663 subjects with COPD (mean age: 62.7 years; 89% white; 65% male across all treatments, including placebo) received at least 1 inhalation dose of umeclidinium at doses of 62.5 or 125 mcg. In the 4 randomized, double-blind, placebo- or active-controlled, efficacy clinical trials, 1,185 subjects received umeclidinium for up to 24 weeks, of which 487 subjects received the recommended dose of umeclidinium 62.5 mcg. In a 12-month, randomized, double-blind, placebo-controlled, long-term safety trial, 227 subjects received umeclidinium 125 mcg for up to 52 weeks [see Clinical Studies (14)].

The incidence of adverse reactions associated with INCRUSE ELLIPTA in Table 1 is based upon 2 placebo-controlled trials: one 24-week trial (Trial 1) and one 12-week trial (Trial 2) [see Clinical Studies (14.2)].

Table 1. Adverse Reactions with INCRUSE ELLIPTA with ≥1% Incidence and More Common than Placebo in Subjects with Chronic Obstructive Pulmonary Disease
Adverse Reaction | INCRUSE ELLIPTA; (n = 487); % | Placebo; (n = 348); %
Infections and infestations
Nasopharyngitis | 8% | 7%
Upper respiratory tract infection | 5% | 4%
Pharyngitis | 1% | <1%
Viral upper respiratory tract infection | 1% | <1%
Respiratory, thoracic, and mediastinal disorders
Cough | 3% | 2%
Musculoskeletal and connective tissue disorders
Arthralgia | 2% | 1%
Myalgia | 1% | <1%
Gastrointestinal disorders
Abdominal pain upper | 1% | <1%
Toothache | 1% | <1%
Injury, poisoning, and procedural complications
Contusion | 1% | <1%
Cardiac disorders
Tachycardia | 1% | <1%

Other adverse reactions with INCRUSE ELLIPTA observed with an incidence <1% but more common than placebo included atrial fibrillation.

In a long-term safety trial (Trial 3), 336 subjects (n = 227 umeclidinium 125 mcg, n = 109 placebo) were treated for up to 52 weeks with umeclidinium 125 mcg or placebo. The demographic and baseline characteristics of the long-term safety trial were similar to those of the efficacy trials described above. Adverse reactions that occurred with a frequency ≥1% in subjects receiving umeclidinium 125 mcg that exceeded that in placebo in this trial were: nasopharyngitis, upper respiratory tract infection, urinary tract infection, pharyngitis, pneumonia, lower respiratory tract infection, rhinitis, supraventricular tachycardia, supraventricular extrasystoles, sinus tachycardia, idioventricular rhythm, headache, dizziness, sinus headache, cough, back pain, arthralgia, pain in extremity, neck pain, myalgia, nausea, dyspepsia, diarrhea, rash, depression, and vertigo.

The safety and efficacy of INCRUSE ELLIPTA in combination with an inhaled corticosteroid/long-acting beta2-adrenergic agonist (ICS/LABA) were also evaluated in four 12‑week clinical trials (Trial 4, Trial 5, Trial 6, and Trial 7). A total of 1,637 subjects with COPD across four 12‑week, randomized, double-blind clinical trials received at least 1 dose of INCRUSE ELLIPTA (62.5 mcg) or placebo administered once daily in addition to background ICS/LABA (mean age: 64 years, 88% white, 65% male across all treatments). Two trials (Trials 4 and 5) evaluated INCRUSE ELLIPTA in combination with fluticasone furoate/vilanterol (FF/VI) 100 mcg/25mcg administered once daily, and 2 trials (Trials 6 and 7) evaluated INCRUSE ELLIPTA administered once daily in combination with fluticasone propionate/salmeterol (FP/SAL) 250 mcg/50 mcg administered twice daily [see Clinical Studies (14.3)]. Adverse reactions that occurred with INCRUSE ELLIPTA in combination with an ICS/LABA were similar to those reported with INCRUSE ELLIPTA as monotherapy. In addition to the umeclidinium monotherapy adverse reactions reported above, adverse reactions occurring with INCRUSE ELLIPTA in combination with an ICS/LABA, at an incidence of ≥1% and exceeding ICS/LABA alone, were oropharyngeal pain and dysgeusia.

6.2 Postmarketing Experience

In addition to adverse reactions reported from clinical trials, the following adverse reactions have been identified during postapproval use of INCRUSE ELLIPTA. Because these reactions are reported voluntarily from a population of uncertain size, it is not always possible to reliably estimate their frequency or establish a causal relationship to drug exposure. These events have been chosen for inclusion due to either their seriousness, frequency of reporting, or causal connection to INCRUSE ELLIPTA or a combination of these factors.

Eye Disorders

Eye pain, glaucoma, vision blurred.

Immune System Disorders

Hypersensitivity reactions, including anaphylaxis, angioedema, pruritus, and urticaria.

Renal and Urinary Disorders

Dysuria, urinary retention.

Respiratory, Thoracic and Mediastinal Disorders

Dysphonia, oropharyngeal pain.

7 DRUG INTERACTIONS

7.1 Anticholinergics

There is potential for an additive interaction with concomitantly used anticholinergic medicines. Therefore, avoid coadministration of INCRUSE ELLIPTA with other anticholinergic-containing drugs as this may lead to an increase in anticholinergic adverse effects [see Warnings and Precautions (5.4, 5.5)].

8 USE IN SPECIFIC POPULATIONS

8.1 Pregnancy

Risk Summary

There are insufficient data on the use of umeclidinium in pregnant women to inform a drug‑associated risk. Umeclidinium administered via inhalation or subcutaneously to pregnant rats and rabbits was not associated with adverse effect on embryofetal development at exposures approximately 50 and 200 times, respectively, the human exposure at the maximum recommended human daily inhaled dose (MRHDID). (See Data.)

The estimated risk of major birth defects and miscarriage for the indicated populations is unknown. In the U.S. general population, the estimated risk of major birth defects and miscarriage in clinically recognized pregnancies is 2% to 4% and 15% to 20%, respectively.

Data

Animal Data: In separate embryofetal developmental studies, pregnant rats and rabbits received umeclidinium during the period of organogenesis at doses up to approximately 50 and 200 times the MRHDID, respectively (on an AUC basis at maternal inhalation doses up to 278 mcg/kg/day in rats and at maternal subcutaneous doses up to 180 mcg/kg/day in rabbits). No evidence of teratogenic effects was observed in either species.

In a perinatal and postnatal developmental study in rats, dams received umeclidinium during late gestation and lactation periods with no evidence of effects on offspring development at doses up to approximately 26 times the MRHDID (on an AUC basis at maternal subcutaneous doses up to 60 mcg/kg/day).

8.2 Lactation

Risk Summary

There is no information available on the presence of umeclidinium in human milk, the effects on the breastfed child, or the effects on milk production. Umeclidinium was detected in the plasma of offspring of lactating rats treated with umeclidinium suggesting its presence in maternal milk. (See Data.) The developmental and health benefits of breastfeeding should be considered along with the mother’s clinical need for INCRUSE ELLIPTA and any potential adverse effects on the breastfed child from umeclidinium or from the underlying maternal condition.

Data

Subcutaneous administration of umeclidinium to lactating rats at greater than or equal to 60 mcg/kg/day resulted in a quantifiable level of umeclidinium in 2 of 54 pups, which may indicate transfer of umeclidinium in milk.

8.4 Pediatric Use

The safety and effectiveness of INCRUSE ELLIPTA have not been established in pediatric patients. INCRUSE ELLIPTA is not indicated for use in pediatric patients.

8.5 Geriatric Use

Based on available data, no adjustment of the dosage of INCRUSE ELLIPTA in geriatric patients is necessary, but greater sensitivity in some older individuals cannot be ruled out.

Clinical trials of INCRUSE ELLIPTA included 810 subjects aged 65 years and older, and, of those, 183 subjects were aged 75 years and older. No overall differences in safety or effectiveness were observed between these subjects and younger subjects, and other reported clinical experience has not identified differences in responses between the elderly and younger subjects.

8.6 Hepatic Impairment

Patients with moderate hepatic impairment (Child-Pugh score of 7-9) showed no relevant increases in Cmax or AUC, nor did protein binding differ between subjects with moderate hepatic impairment and their healthy controls. Studies in subjects with severe hepatic impairment have not been performed [see Clinical Pharmacology (12.3)].

8.7 Renal Impairment

Patients with severe renal impairment (CrCl <30 mL/min) showed no relevant increases in Cmax or AUC, nor did protein binding differ between subjects with severe renal impairment and their healthy controls. No dosage adjustment is required in patients with renal impairment [see Clinical Pharmacology (12.3)].

10 OVERDOSAGE

High doses of umeclidinium may lead to anticholinergic signs and symptoms.

Treatment of overdosage consists of discontinuation of INCRUSE ELLIPTA together with institution of appropriate symptomatic and/or supportive therapy.

11 DESCRIPTION

INCRUSE ELLIPTA is an inhalation powder drug product for delivery of umeclidinium (an anticholinergic) to patients by oral inhalation.

Umeclidinium bromide has the chemical name 1-[2-(benzyloxy)ethyl]-4-(hydroxydiphenylmethyl)-1-azoniabicyclo[2.2.2]octane bromide and the following chemical structure:

Umeclidinium bromide is a white powder with a molecular weight of 508.5, and the empirical formula is C29H34NO2•Br (as a quaternary ammonium bromide compound). It is slightly soluble in water.

INCRUSE ELLIPTA is a light grey and light green plastic inhaler containing a foil blister strip. Each blister on the strip contains a white powder blend of micronized umeclidinium bromide (74.2 mcg equivalent to 62.5 mcg of umeclidinium), magnesium stearate (75 mcg), and lactose monohydrate (to 12.5 mg). The lactose monohydrate contains milk proteins. After the inhaler is activated, the powder within the blister is exposed and ready for dispersion into the airstream created by the patient inhaling through the mouthpiece.

Under standardized in vitro test conditions, INCRUSE ELLIPTA delivers 55 mcg of umeclidinium per dose when tested at a flow rate of 60 L/min for 4 seconds.

In adult subjects with obstructive lung disease and severely compromised lung function (COPD with forced expiratory volume in 1 second/forced vital capacity [FEV1/FVC] <70% and FEV1 <30% predicted or FEV1 <50% predicted plus chronic respiratory failure), mean peak inspiratory flow through the ELLIPTA inhaler was 67.5 L/min (range: 41.6 to 83.3 L/min).

The actual amount of drug delivered to the lung will depend on patient factors, such as inspiratory flow profile.

12 CLINICAL PHARMACOLOGY

12.1 Mechanism of Action

Umeclidinium is a long-acting muscarinic antagonist, which is often referred to as an anticholinergic. It has similar affinity to the subtypes of muscarinic receptors M1 to M5. In the airways, it exhibits pharmacological effects through inhibition of M3 receptors at the smooth muscle leading to bronchodilation. The competitive and reversible nature of antagonism was shown with human and animal origin receptors and isolated organ preparations. In preclinical in vitro as well as in vivo studies, prevention of methacholine- and acetylcholine-induced bronchoconstrictive effects was dose-dependent and lasted longer than 24 hours. The clinical relevance of these findings is unknown. The bronchodilation following inhalation of umeclidinium is predominantly a site-specific effect.

12.2 Pharmacodynamics

Cardiac Electrophysiology

QTc interval prolongation was studied in a double-blind, multiple-dose, placebo- and positive-controlled, crossover study in 86 healthy subjects. Following repeat doses of umeclidinium 500 mcg once daily (8 times the recommended dosage) for 10 days, umeclidinium does not prolong QTc to any clinically relevant extent.

12.3 Pharmacokinetics

Linear pharmacokinetics was observed for umeclidinium (62.5 to 500 mcg).

Absorption

Umeclidinium plasma levels may not predict therapeutic effect. Following inhaled administration of umeclidinium in healthy subjects, Cmax occurred at 5 to 15 minutes. Umeclidinium is mostly absorbed from the lung after inhaled doses with minimum contribution from oral absorption. Following repeat dosing of inhaled INCRUSE ELLIPTA, steady state was achieved within 14 days with up to 1.8-fold accumulation.

Distribution

Following intravenous administration to healthy subjects, the mean volume of distribution was 86 L. In vitro plasma protein binding in human plasma was on average 89%.

Elimination

Metabolism: In vitro data showed that umeclidinium is primarily metabolized by the enzyme cytochrome P450 2D6 (CYP2D6) and is a substrate for the P-glycoprotein (P-gp) transporter. The primary metabolic routes for umeclidinium are oxidative (hydroxylation, O-dealkylation) followed by conjugation (e.g., glucuronidation), resulting in a range of metabolites with either reduced pharmacological activity or for which the pharmacological activity has not been established. Systemic exposure to the metabolites is low.

Excretion: The effective half-life after once-daily orally inhaled dosing is 11 hours. Following intravenous dosing with radiolabeled umeclidinium, mass balance showed 58% of the radiolabel in the feces and 22% in the urine. The excretion of the drug-related material in the feces following intravenous dosing indicated elimination in the bile. Following oral dosing to healthy male subjects, radiolabel recovered in feces was 92% of the total dose and that in urine was <1% of the total dose, suggesting negligible oral absorption.

Specific Populations

Population pharmacokinetic analysis showed no evidence of a clinically significant effect of age (40 to 93 years) (Figure 1), gender (69% male) (Figure 1), inhaled corticosteroid use (48%), or weight (34 to 161 kg) on systemic exposure of umeclidinium. In addition, there was no evidence of a clinically significant effect of race.

Patients with Hepatic Impairment: The impact of hepatic impairment on the pharmacokinetics of INCRUSE ELLIPTA has been evaluated in subjects with moderate hepatic impairment (Child-Pugh score of 7-9). There was no evidence of an increase in systemic exposure to umeclidinium (Cmax and AUC) (Figure 1). There was no evidence of altered protein binding in subjects with moderate hepatic impairment compared with healthy subjects. INCRUSE ELLIPTA has not been evaluated in subjects with severe hepatic impairment.

Patients with Renal Impairment: The pharmacokinetics of INCRUSE ELLIPTA has been evaluated in subjects with severe renal impairment (CrCl <30 mL/min). There was no evidence of an increase in systemic exposure to umeclidinium (Cmax and AUC) (Figure 1). There was no evidence of altered protein binding in subjects with severe renal impairment compared with healthy subjects.

Figure 1. Impact of Intrinsic and Extrinsic Factors on the Systemic Exposure of Umeclidinium

Drug Interaction Studies

Umeclidinium and P-glycoprotein Transporter: Umeclidinium is a substrate of P-gp. The effect of the moderate P-gp transporter inhibitor verapamil (240 mg once daily) on the steady-state pharmacokinetics of umeclidinium was assessed in healthy subjects. No effect on umeclidinium Cmax was observed; however, an approximately 1.4-fold increase in umeclidinium AUC was observed (Figure 1).

Umeclidinium and Cytochrome P450 2D6: In vitro metabolism of umeclidinium is mediated primarily by CYP2D6. However, no clinically meaningful difference in systemic exposure to umeclidinium (500 mcg) (8 times the approved dose) was observed following repeat daily inhaled dosing to normal (ultrarapid, extensive, and intermediate metabolizers) and CYP2D6 poor metabolizer subjects (Figure 1).

13 NONCLINICAL TOXICOLOGY

13.1 Carcinogenesis, Mutagenesis, Impairment of Fertility

Umeclidinium produced no treatment-related increases in the incidence of tumors in 2-year inhalation studies in rats and mice at inhaled doses up to 137 and 295/200 mcg/kg/day (male/female), respectively (approximately 20 and 25/20 times, respectively, the MRHDID for adults on an AUC basis).

Umeclidinium tested negative in the following genotoxicity assays: the in vitro Ames assay, in vitro mouse lymphoma assay, and in vivo rat bone marrow micronucleus assay.

No evidence of impairment of fertility was observed in male and female rats at subcutaneous doses up to 180 mcg/kg/day and at inhaled doses up to 294 mcg/kg/day, respectively (approximately 100 and 50 times, respectively, the MRHDID for adults on an AUC basis).

14 CLINICAL STUDIES

The safety and efficacy of umeclidinium 62.5 mcg were evaluated in 3 dose-ranging trials, 2 placebo-controlled clinical trials (one 12-week trial and one 24-week trial), and a 12-month long‑term safety trial. The efficacy of INCRUSE ELLIPTA is based primarily on the dose‑ranging trials in 624 subjects and the 2 placebo-controlled confirmatory trials in 1,738 subjects with COPD, including chronic bronchitis and/or emphysema. [See Clinical Studies (14.1, 14.2).]

The safety and efficacy of INCRUSE ELLIPTA in combination with an ICS/LABA were also evaluated in four 12-week clinical trials. The efficacy of INCRUSE ELLIPTA in combination with an ICS/LABA is based on 1,637 subjects with COPD. [See Clinical Studies (14.3).]

Evidence of efficacy for INCRUSE ELLIPTA on COPD exacerbations was established by the efficacy of the umeclidinium component as part of a fixed-dose combination with an ICS/LABA, as assessed in a 12-month trial in 10,355 subjects. [See Clinical Studies (14.3).]

14.1 Dose-Ranging Trials

Dose selection for umeclidinium in COPD was supported by a 7-day, randomized, double-blind, placebo-controlled, crossover trial evaluating 4 doses of umeclidinium (15.6 to 125 mcg) or placebo dosed once daily in the morning in 163 subjects with COPD. A dose ordering was observed, with the 62.5- and 125-mcg doses demonstrating larger improvements in FEV1 over 24 hours compared with the lower doses of 15.6 and 31.25 mcg (Figure 2).

The differences in trough FEV1 from baseline after 7 days for placebo and the 15.6-, 31.25-, 62.5-, and 125-mcg doses were -74 mL (95% CI: -118, -31), 38 mL (95% CI: -6, 83), 27 mL (95% CI: -18, 72), 49 mL (95% CI: 6, 93), and 109 mL (95% CI: 65, 152), respectively. Two additional dose-ranging trials in subjects with COPD demonstrated minimal additional benefit at doses above 125 mcg. The dose-ranging results supported the evaluation of 2 doses of umeclidinium, 62.5 and 125 mcg, in the confirmatory COPD trials to further assess dose response.

Evaluations of dosing interval by comparing once- and twice-daily dosing supported selection of a once-daily dosing interval for further evaluation in the confirmatory COPD trials.

Figure 2. Adjusted Mean Change from Baseline in Postdose Serial FEV1 (mL) on Days 1 and 7

Day 1

Day 7

14.2 Maintenance Treatment: Confirmatory Trials

Lung Function

The clinical development program for INCRUSE ELLIPTA included 2 randomized, double‑blind, placebo-controlled, parallel-group trials in subjects with COPD designed to evaluate the efficacy of INCRUSE ELLIPTA on lung function. Trial 1 (NCT01313650) was a 24-week placebo‑controlled trial, and Trial 2 (NCT01387230) was a 12-week placebo‑controlled trial. These trials treated subjects that had a clinical diagnosis of COPD, were 40 years of age or older, had a history of smoking ≥10 pack-years, had a post-albuterol FEV1 ≤70% of predicted normal values, had a ratio of FEV1/FVC of <0.7, and had a Modified Medical Research Council (mMRC) score ≥2. Subjects in Trial 1 had a mean age of 63 years and an average smoking history of 46 pack-years, with 50% identified as current smokers. At screening, the mean postbronchodilator percent predicted FEV1 was 47% (range: 13% to 74%), the mean postbronchodilator FEV1/FVC ratio was 0.47 (range: 0.20 to 0.74), and the mean percent reversibility was 15% (range: -35% to 109%). The majority of subjects (72%) reported not having a COPD exacerbation in the prior 12 months. Baseline demographics and lung function for subjects in Trial 2 were similar to those in Trial 1.

Trial 1 evaluated umeclidinium 62.5 mcg and placebo. The primary endpoint was change from baseline in trough (predose) FEV1 at Day 169 (defined as the mean of the FEV1 values obtained at 23 and 24 hours after the previous dose on Day 168) compared with placebo. INCRUSE ELLIPTA 62.5 mcg demonstrated a larger increase in mean change from baseline in trough (predose) FEV1 relative to placebo (Table 2). Similar results were obtained from Trial 2.

Table 2. Least Squares Mean Change from Baseline in Trough FEV1 (mL) at Day 169 in the Intent-to-Treat Population (Trial 1)
Treatment | n | Trough FEV1 (mL) at Day 169
Treatment | n | Difference from Placebo; (95% CI); n = 280
INCRUSE ELLIPTA | n = 418 | 115 (76, 155)
n = Number in intent-to-treat population.

Serial spirometric evaluations throughout the 24-hour dosing interval were performed in a subset of subjects (n = 54, umeclidinium 62.5 mcg; n = 36, placebo) at Days 1, 84, and 168 in Trial 1, and for all patients at Days 1 and 84 in Trial 2. Results from Trial 1 at Day 1 and Day 168 are shown in Figure 3.

Figure 3. Least Squares (LS) Mean Change from Baseline in FEV1 (mL) over Time (0-24 h) on Days 1 and 168 (Trial 1 Subset Population)

Day 1

Day 168

In Trial 1, the mean peak FEV1 (over the first 6 hours relative to baseline) at Day 1 and at Day 168 for the group receiving umeclidinium 62.5 mcg compared with placebo was 126 and 130 mL, respectively.

Health-Related Quality of Life

Health-related quality of life was measured using St. George’s Respiratory Questionnaire (SGRQ). Umeclidinium demonstrated an improvement in mean SGRQ total score compared with placebo treatment at Day 168: -4.69 (95% CI: -7.07,-2.31). The proportion of patients with a clinically meaningful decrease (defined as a decrease of at least 4 units from baseline) at Week 24 was greater for INCRUSE ELLIPTA 62.5 mcg (42%; 172/410) compared with placebo (31%; 86/274).

14.3 Maintenance Treatment: Combination with an ICS/LABA Trials

Lung Function

The efficacy of INCRUSE ELLIPTA in combination with an ICS/LABA was evaluated in 4 randomized, double-blind, parallel-group trials in subjects with COPD. These trials, all of similar study design, were of 12-weeks’ treatment duration. Subjects were randomized to INCRUSE ELLIPTA 62.5 mcg + ICS/LABA or placebo + ICS/LABA. Entry criteria for subjects enrolled in these trials were similar to those described above in Section 14.2. The primary endpoint for these trials was change from baseline in trough (predose) FEV1 at Day 85 (defined as the mean of the FEV1 values obtained at 23 and 24 hours after the previous dose on Day 84). Baseline FEV1 was measured while subjects were on background ICS/LABA.

Combination with Fluticasone Furoate + Vilanterol

Trial 4 (NCT01957163) and Trial 5 (NCT02119286) randomized subjects to INCRUSE ELLIPTA 62.5 mcg + FF/VI 100 mcg/25 mcg administered once daily or placebo + FF/VI 100 mcg/25 mcg administered once daily. Trial population demographics and results for Trials 4 and 5 were similar; therefore, only Trial 4 results are presented below.

Subjects in Trial 4 across all treatment arms had a mean age of 64 years and an average smoking history of 50 pack-years, with 42% identified as current smokers. At screening, the mean postbronchodilator percent predicted FEV1 was 45% (range: 13% to 76%), the mean postbronchodilator FEV1/FVC ratio was 0.48 (range: 0.22 to 0.70), and the mean percent reversibility was 14% (range: -20% to 71%). The majority of subjects (85%) reported not having a COPD exacerbation in the prior 12 months.

The primary endpoint was change from baseline in trough (predose) FEV1 at Day 85 (defined as the mean of the FEV1 values obtained at 23 and 24 hours after the previous dose on Day 84) compared with placebo (INCRUSE ELLIPTA + FF/VI vs. placebo + FF/VI). INCRUSE ELLIPTA + FF/VI demonstrated a larger mean change from baseline in trough (predose) FEV1 relative to placebo + FF/VI (Table 3).

Table 3. Least Squares Mean Change from Baseline in Trough FEV1 (mL) at Day 85 in the Intent-to-Treat Population (Trial 4)
Treatment | n | Trough FEV1 (mL) at Day 85
Treatment | n | Difference from Placebo + FF/VI; (95% CI); n = 206
INCRUSE ELLIPTA + FF/VI | n = 206 | 124 (93, 154)
FF/VI = fluticasone furoate/vilanterol.
n = Number in intent-to-treat population.

Combination with Fluticasone Propionate + Salmeterol

Trial 6 (NCT01772134) and Trial 7 (NCT01772147) randomized subjects to INCRUSE ELLIPTA 62.5 mcg + FP/SAL 250 mcg/50 mcg or placebo + FP/SAL 250 mcg/50 mcg. The treatments with INCRUSE ELLIPTA and placebo were administered once daily, while the FP/SAL treatment was administered twice daily. Trial population demographics and results for Trials 6 and 7 were similar; therefore, only Trial 6 results are presented below.

Subjects in Trial 6 across all treatment arms had a mean age of 63 years and an average smoking history of 50 pack-years, with 54% identified as current smokers. At screening, the mean postbronchodilator percent predicted FEV1 was 47% (range: 12% to 70%), the mean postbronchodilator FEV1/FVC ratio was 0.47 (range: 0.22 to 0.69), and the mean percent reversibility was 16% (range: -36% to 79%). The majority of subjects (79%) reported not having a COPD exacerbation in the prior 12 months.

The primary endpoint was change from baseline in trough (predose) FEV1 at Day 85 (defined as the mean of the FEV1 values obtained at 23 and 24 hours after the previous dose on Day 84) compared with placebo (INCRUSE ELLIPTA + FP/SAL vs. placebo + FP/SAL). INCRUSE ELLIPTA + FP/SAL demonstrated a larger mean change from baseline in trough (predose) FEV1 relative to placebo + FP/SAL (Table 4).

Table 4. Least Squares Mean Change from Baseline in Trough FEV1 (mL) at Day 85 in the Intent-to-Treat Population (Trial 6)
Treatment | n | Trough FEV1 (mL) at Day 85
Treatment | n | Difference from Placebo + FP/SAL; (95% CI); n = 205
INCRUSE ELLIPTA+FP/SAL | n = 204 | 147 (107, 187)
FP/SAL = fluticasone propionate/salmeterol.
n = Number in intent-to-treat population.

Exacerbations

In Trial 8 (NCT02164513), a total of 10,355 subjects with COPD with a history of 1 or more moderate or severe exacerbations in the prior 12 months were randomized (2:2:1) to receive fluticasone furoate/umeclidinium/vilanterol 100 mcg/62.5 mcg/25 mcg (n = 4,151), fluticasone furoate/vilanterol 100 mcg/25 mcg (n = 4,133), or umeclidinium/vilanterol 62.5 mcg/25 mcg (n = 2,070) administered once daily in a 12-month trial. The population demographics across all treatments were: mean age of 65 years, 77% white, 66% male, and an average smoking history of 46.6 pack-years, with 35% identified as current smokers. At trial entry, the most common COPD medications were ICS + anticholinergic + LABA (34%), ICS + LABA (26%), anticholinergic + LABA (8%), and anticholinergic (7%). The mean postbronchodilator percent predicted FEV1 was 46% (standard deviation: 15%), the mean postbronchodilator FEV1/FVC ratio was 0.47 (standard deviation: 0.12), and the mean percent reversibility was 10% (range: -59% to 125%).

The primary endpoint was annual rate of on-treatment moderate and severe exacerbations in subjects treated with fluticasone furoate/umeclidinium/vilanterol compared with the fixed-dose combinations of fluticasone furoate/vilanterol and umeclidinium/vilanterol. Exacerbations were defined as worsening of 2 or more major symptoms (dyspnea, sputum volume, and sputum purulence) or worsening of any 1 major symptom together with any 1 of the following minor symptoms: sore throat, colds (nasal discharge and/or nasal congestion), fever without other cause, and increased cough or wheeze for at least 2 consecutive days. Exacerbations were considered to be of moderate severity if treatment with systemic corticosteroids and/or antibiotics was required and were considered to be severe if resulted in hospitalization or death.

Evidence of efficacy for INCRUSE ELLIPTA on COPD exacerbations was established by the efficacy of the umeclidinium component of fluticasone furoate/umeclidinium/vilanterol in Trial 8. Treatment with fluticasone furoate/umeclidinium/vilanterol statistically significantly reduced the on-treatment annual rate of moderate/severe exacerbations by 15% compared with fluticasone furoate/vilanterol (Table 5). A reduction in risk of on-treatment moderate/severe exacerbation (as measured by time to first) was also observed for the same comparison.

Table 5. Moderate and Severe Chronic Obstructive Pulmonary Disease Exacerbations (Trial 8)
Treatment | n | Mean Annual Rate; (exacerbations/year) | FF/UMEC/VI Rate Ratio vs. Comparator; (95% CI) | % Reduction in Exacerbation Rate; (95% CI) | P Value
FF/UMEC/VI | 4,145 | 0.91
FF/VI | 4,133 | 1.07 | 0.85; (0.80, 0.90) | 15; (10, 20) | P<0.001
UMEC/VI | 2,069 | 1.21 | 0.75; (0.70, 0.81) | 25; (19, 30) | P<0.001
FF/UMEC/VI = Fluticasone furoate/umeclidinium/vilanterol 100 mcg/62.5 mcg/25 mcg, FF/VI = Fluticasone furoate/vilanterol 100 mcg/25 mcg, UMEC/VI = Umeclidinium/vilanterol 62.5 mcg/25 mcg.
a On-treatment analyses excluded exacerbation data collected after discontinuation of study treatment.

16 HOW SUPPLIED/STORAGE AND HANDLING

INCRUSE ELLIPTA is supplied as a disposable light grey and light green plastic inhaler containing a foil strip with 30 blisters (NDC 0173-0873-10) or 7 blisters (institutional pack) (NDC 0173-0873-06).

The inhaler is packaged in a moisture-protective foil tray with a desiccant and a peelable lid.

Store at room temperature between 68°F and 77°F (20°C and 25°C); excursions permitted from 59°F to 86°F (15°C to 30°C) [See USP Controlled Room Temperature]. Store in a dry place away from direct heat or sunlight. Keep out of reach of children.

INCRUSE ELLIPTA should be stored inside the unopened moisture-protective foil tray and only removed from the tray immediately before initial use. Discard INCRUSE ELLIPTA 6 weeks after opening the foil tray or when the counter reads “0” (after all blisters have been used), whichever comes first. The inhaler is not reusable. Do not attempt to take the inhaler apart.

17 PATIENT COUNSELING INFORMATION

Advise the patient to read the FDA-approved patient labeling (Patient Information and Instructions for Use).

Not for Acute Symptoms

Inform patients that INCRUSE ELLIPTA is not meant to relieve acute symptoms of COPD and extra doses should not be used for that purpose. Advise patients to treat acute symptoms with an inhaled, short-acting beta2-agonist such as albuterol. Provide patients with such medication and instruct them in how it should be used.

Instruct patients to seek medical attention immediately if they experience any of the following:

- Decreasing effectiveness of inhaled, short-acting beta2-agonists
- Need for more inhalations than usual of inhaled, short-acting beta2-agonists
- Significant decrease in lung function as outlined by the physician

Tell patients they should not stop therapy with INCRUSE ELLIPTA without physician/provider guidance since symptoms may recur after discontinuation. [See Warnings and Precautions (5.1).]

Paradoxical Bronchospasm

As with other inhaled medicines, INCRUSE ELLIPTA can cause paradoxical bronchospasm. If paradoxical bronchospasm occurs, instruct patients to discontinue INCRUSE ELLIPTA and contact their healthcare provider right away. [See Warnings and Precautions (5.2).]

Worsening of Narrow-Angle Glaucoma

Instruct patients to be alert for signs and symptoms of acute narrow-angle glaucoma (e.g., eye pain or discomfort, blurred vision, visual halos or colored images in association with red eyes from conjunctival congestion and corneal edema). Instruct patients to consult a physician immediately if any of these signs or symptoms develop. [See Warnings and Precautions (5.4).]

Worsening of Urinary Retention

Instruct patients to be alert for signs and symptoms of urinary retention (e.g., difficulty passing urine, painful urination). Instruct patients to consult a physician immediately if any of these signs or symptoms develop. [See Warnings and Precautions (5.5).]

Trademarks are owned by or licensed to the GSK group of companies.

GlaxoSmithKline
Durham, NC 27701

©2023 GSK group of companies or its licensor.

INC:10PI

PATIENT INFORMATION

INCRUSE ELLIPTA (IN-cruise e-LIP-ta)

(umeclidinium inhalation powder)

for oral inhalation use

What is INCRUSE ELLIPTA?

- INCRUSE ELLIPTA is an anticholinergic medicine (umeclidinium).
- Anticholinergic medicines such as umeclidinium help the muscles around the airways in your lungs stay relaxed to prevent symptoms such as wheezing, cough, chest tightness, and shortness of breath. These symptoms can happen when the muscles around the airways tighten. This makes it hard to breathe.
- INCRUSE ELLIPTA is not used to relieve sudden breathing problems and will not replace a rescue inhaler.
- INCRUSE ELLIPTA is a prescription medicine used long term (chronic) to treat people with chronic obstructive pulmonary disease (COPD). COPD is a chronic lung disease that includes chronic bronchitis, emphysema, or both.
- INCRUSE ELLIPTA is used as 1 inhalation 1 time each day to improve symptoms of COPD for better breathing and to reduce the number of flare-ups (the worsening of your COPD symptoms for several days).
- INCRUSE ELLIPTA should not be used in children. It is not known if INCRUSE ELLIPTA is safe and effective in children.

Do not use INCRUSE ELLIPTA if you:

- have a severe allergy to milk proteins. Ask your healthcare provider if you are not sure.
- are allergic to umeclidinium or any of the ingredients in INCRUSE ELLIPTA. See the end of this Patient Information for a complete list of ingredients in INCRUSE ELLIPTA.

Before using INCRUSE ELLIPTA, tell your healthcare provider about all of your medical conditions, including if you:

- have heart problems.
- have eye problems such as glaucoma. INCRUSE ELLIPTA may make your glaucoma worse.
- are allergic to milk proteins.
- have prostate or bladder problems, or problems passing urine. INCRUSE ELLIPTA may make these problems worse.
- are pregnant or plan to become pregnant. It is not known if INCRUSE ELLIPTA may harm your unborn baby.
- are breastfeeding or plan to breastfeed. It is not known if the medicine in INCRUSE ELLIPTA passes into your breast milk and if it can harm your baby.

Tell your healthcare provider about all the medicines you take, including prescription and over-the-counter medicines, vitamins, and herbal supplements. INCRUSE ELLIPTA and certain other medicines may interact with each other. This may cause serious side effects.

Especially tell your healthcare provider if you take:

- anticholinergics (including tiotropium, ipratropium, aclidinium)
- atropine

Know the medicines you take. Keep a list of them to show your healthcare provider and pharmacist when you get a new medicine.

How should I use INCRUSE ELLIPTA?

Read the step-by-step instructions for using INCRUSE ELLIPTA at the end of this Patient Information.

- Do not use INCRUSE ELLIPTA unless your healthcare provider has taught you how to use the inhaler and you understand how to use it correctly.
- Use INCRUSE ELLIPTA exactly as your healthcare provider tells you to use it. Do not use INCRUSE ELLIPTA more often than prescribed.
- Use 1 inhalation of INCRUSE ELLIPTA 1 time each day. Use INCRUSE ELLIPTA at the same time each day.
- If you miss a dose of INCRUSE ELLIPTA, take it as soon as you remember. Do not take more than 1 inhalation per day. Take your next dose at your usual time. Do not take 2 doses at 1 time.
- If you take too much INCRUSE ELLIPTA, call your healthcare provider or go to the nearest hospital emergency room right away if you have any unusual symptoms, such as worsening shortness of breath, chest pain, increased heart rate, or shakiness.
- Do not use other medicines that contain an anticholinergic for any reason. Ask your healthcare provider or pharmacist if any of your other medicines are anticholinergic medicines.
- Do not stop using INCRUSE ELLIPTA unless told to do so by your healthcare provider because your symptoms might get worse. Your healthcare provider will change your medicines as needed.
- Talk to your healthcare provider right away if you stop using INCRUSE ELLIPTA.
- INCRUSE ELLIPTA does not relieve sudden symptoms of COPD and you should not take extra doses of INCRUSE ELLIPTA to relieve these sudden symptoms. Always have a rescue inhaler with you to treat sudden symptoms. If you do not have a rescue inhaler, call your healthcare provider to have one prescribed for you.
- Call your healthcare provider or get medical care right away if:
  - your breathing problems get worse.
  - you need to use your rescue inhaler more often than usual.
  - your rescue inhaler does not work as well to relieve your symptoms.

What are the possible side effects of INCRUSE ELLIPTA?

INCRUSE ELLIPTA can cause serious side effects, including:

- sudden breathing problems immediately after inhaling your medicine. If you have sudden breathing problems immediately after inhaling your medicine, stop using INCRUSE ELLIPTA and call your healthcare provider right away.
- serious allergic reactions (anaphylaxis). Stop using INCRUSE ELLIPTA and call your healthcare provider or go to the nearest emergency room right away if you get any of the following symptoms of a serious allergic reaction:

○rash
○hives
○severe itching

○swelling of your face, mouth, and tongue
○breathing problems

- new or worsening eye problems including acute narrow-angle glaucoma. You should have regular eye exams while using INCRUSE ELLIPTA. Acute narrow-angle glaucoma can cause permanent loss of vision if not treated. Symptoms of acute narrow-angle glaucoma may include:

○eye pain or discomfort
○nausea or vomiting
○blurred vision

○seeing halos or bright colors around lights
○red eyes

If you have these symptoms, call your healthcare provider right away before taking another dose.

- urinary retention. People who take INCRUSE ELLIPTA may develop new or worse urinary retention. Symptoms of urinary retention may include:

○difficulty urinating
○painful urination

○urinating frequently
○urination in a weak stream or drips

If you have these symptoms of urinary retention, stop taking INCRUSE ELLIPTA, and call your healthcare provider right away before taking another dose.

Common side effects of INCRUSE ELLIPTA include:

- upper respiratory tract infection
- stuffy or runny nose
- cough
- mouth and throat pain
- joint pain
- change in taste

- muscle pain
- tooth pain
- stomach pain
- bruising or dark areas of skin
- fast or irregular heartbeat

These are not all the possible side effects of INCRUSE ELLIPTA.

Call your doctor for medical advice about side effects. You may report side effects to FDA at 1-800-FDA-1088.

How should I store INCRUSE ELLIPTA?

- Store INCRUSE ELLIPTA at room temperature between 68°F and 77°F (20°C and 25°C). Keep in a dry place away from heat and sunlight.
- Store INCRUSE ELLIPTA in the unopened tray and only open when ready for use.
- Safely throw away INCRUSE ELLIPTA in the trash 6 weeks after you open the tray or when the counter reads “0”, whichever comes first. Write the date you open the tray on the label on the inhaler.
- Keep INCRUSE ELLIPTA and all medicines out of the reach of children.

General information about the safe and effective use of INCRUSE ELLIPTA.

Medicines are sometimes prescribed for purposes other than those listed in a Patient Information leaflet. Do not use INCRUSE ELLIPTA for a condition for which it was not prescribed. Do not give INCRUSE ELLIPTA to other people, even if they have the same symptoms that you have. It may harm them.

You can ask your healthcare provider or pharmacist for information about INCRUSE ELLIPTA that is written for health professionals.

What are the ingredients in INCRUSE ELLIPTA?

Active ingredient: umeclidinium

Inactive ingredients: lactose monohydrate (contains milk proteins), magnesium stearate

For more information about INCRUSE ELLIPTA, call 1-888-825-5249.

Trademarks are owned by or licensed to the GSK group of companies.

GlaxoSmithKline, Durham, NC 27701

©2023 GSK group of companies or its licensor.

INC:8PIL

This Patient Information has been approved by the U.S. Food and Drug Administration Revised: December 2023

INSTRUCTIONS FOR USE

INCRUSE ELLIPTA (IN-cruise e-LIP-ta)

(umeclidinium inhalation powder)

for oral inhalation use

Read this before you start:

- If you open and close the cover without inhaling the medicine, you will lose the dose.
- The lost dose will be securely held inside the inhaler, but it will no longer be available to be inhaled.
- It is not possible to accidentally take a double dose or an extra dose in 1 inhalation.

Your INCRUSE ELLIPTA inhaler

How to use your inhaler

- INCRUSE ELLIPTA comes in a tray.
- Peel back the lid to open the tray. See Figure A.
- The tray contains a desiccant to reduce moisture. Do not eat or breathe in (inhale). Throw it away in the household trash out of reach of children and pets. See Figure B.

Figure A

Figure B

Important Notes:

- Your inhaler contains 30 doses (7 doses if you have a sample or institutional pack).
- Each time you fully open the cover of the inhaler (you will hear a clicking sound), a dose is ready to be inhaled. This is shown by a decrease in the number on the counter.
- If you open and close the cover without inhaling the medicine, you will lose the dose. The lost dose will be held in the inhaler, but it will no longer be available to be inhaled. It is not possible to accidentally take a double dose or an extra dose in 1 inhalation.
- Do not open the cover of the inhaler until you are ready to use it. To avoid wasting doses after the inhaler is ready, do not close the cover until after you have inhaled the medicine.
- Write the “Tray opened” and “Discard” dates on the inhaler label. The “Discard” date is 6 weeks from the date you open the tray.

Check the counter. See Figure C.

Figure C

- Before the inhaler is used for the first time, the counter should show the number 30 (7 if you have a sample or institutional pack). This is the number of doses in the inhaler.
- Each time you open the cover, you prepare 1 dose of medicine.
- The counter counts down by 1 each time you open the cover.

Prepare your dose:

Wait to open the cover until you are ready to take your dose.

Figure D

Step 1. Open the cover of the inhaler. See Figure D.

- Slide the cover down to expose the mouthpiece. You should hear a “click.” The counter will count down by 1 number. You do not need to shake this kind of inhaler. Your inhaler is now ready to use.
- If the counter does not count down as you hear the click, the inhaler will not deliver the medicine. Call your healthcare provider or pharmacist if this happens.

Figure E

Step 2. Breathe out. See Figure E.

- While holding the inhaler away from your mouth, breathe out (exhale) fully. Do not breathe out into the mouthpiece.

Figure F

Step 3. Inhale your medicine. See Figure F.

- Put the mouthpiece between your lips, and close your lips firmly around it. Your lips should fit over the curved shape of the mouthpiece.
- Take 1 long, steady, deep breath in through your mouth. Do not breathe in through your nose.

Figure G

- Do not block the air vent with your fingers. See Figure G.

Figure H

- Remove the inhaler from your mouth and hold your breath for about 3 to 4 seconds (or as long as comfortable for you). See Figure H.

Figure I

Step 4. Breathe out slowly and gently. See Figure I.

- You may not taste or feel the medicine, even when you are using the inhaler correctly.
- Do not take another dose from the inhaler even if you do not feel or taste the medicine.

Figure J

Step 5. Close the inhaler. See Figure J.

- You can clean the mouthpiece if needed, using a dry tissue, before you close the cover. Routine cleaning is not required.
- Slide the cover up and over the mouthpiece as far as it will go.

Important Note: When should you get a refill?

Figure K

- When you have fewer than 10 doses remaining in your inhaler, the left half of the counter shows red as a reminder to get a refill. See Figure K.
- After you have inhaled the last dose, the counter will show “0” and will be empty.
- Throw the empty inhaler away in your household trash out of reach of children and pets.

For more information about INCRUSE ELLIPTA or how to use your inhaler, call 1-888-825-5249.

Trademarks are owned by or licensed to the GSK group of companies.

GlaxoSmithKline, Durham, NC 27701

©2023 GSK group of companies or its licensor.

INC:3IFU

This Instructions for Use has been approved by the U.S. Food and Drug Administration Revised: December 2023

PACKAGE LABEL

PRINCIPAL DISPLAY PANEL

NDC 0173-0873-10

INCRUSE ELLIPTA

(umeclidinium inhalation powder)

62.5 mcg

Rx Only

FOR ORAL INHALATION ONLY

Each blister contains 62.5 mcg of umeclidinium, magnesium stearate, and lactose monohydrate.

1 ELLIPTA Inhaler containing 1 Foil Strip of 30 Blisters

GSK

Made in Singapore

©2025 GSK group of companies or its licensor

62000000102193 Rev. 10/25